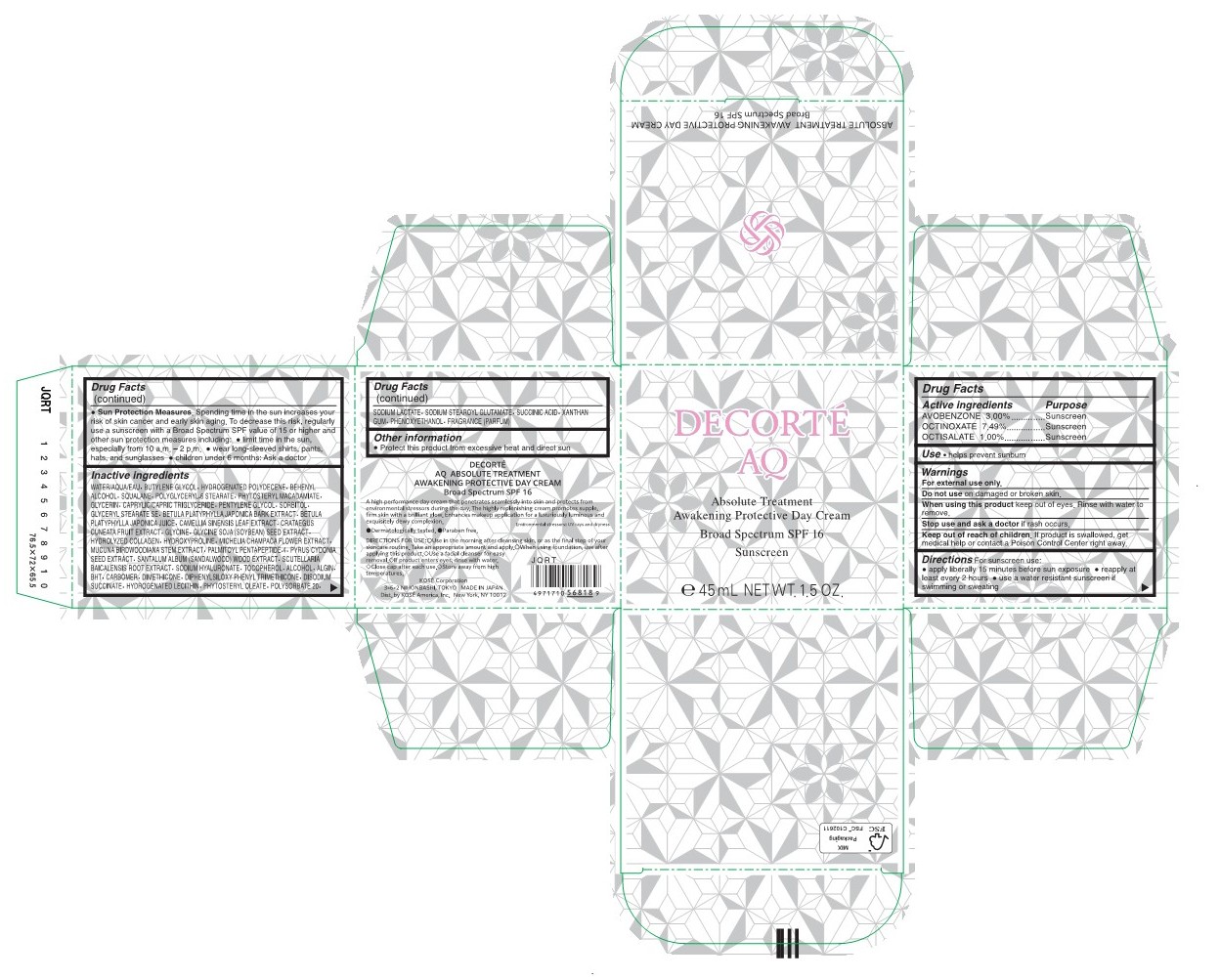 DRUG LABEL: DECORTE AQ ABSOLUTE TREATMENT AWAKENING PROTECTIVE DAY
NDC: 66820-0500 | Form: CREAM
Manufacturer: KOSÉ America, Inc.
Category: otc | Type: HUMAN OTC DRUG LABEL
Date: 20251223

ACTIVE INGREDIENTS: AVOBENZONE 30 mg/1 mL; OCTINOXATE 74.945 mg/1 mL; OCTISALATE 10 mg/1 mL
INACTIVE INGREDIENTS: WATER; BUTYLENE GLYCOL; HYDROGENATED POLYDECENE TYPE I; ALCOHOL; SQUALANE; DOCOSANOL; POLYGLYCERYL-6 STEARATE; PHYTOSTERYL MACADAMIATE; GLYCERIN; MEDIUM-CHAIN TRIGLYCERIDES; PENTYLENE GLYCOL; SORBITOL; GLYCERYL STEARATE SE; DIMETHICONE; PHENOXYETHANOL; BETULA PLATYPHYLLA RESIN; SODIUM STEAROYL GLUTAMATE; HYDROGENATED SOYBEAN LECITHIN; XANTHAN GUM; GLYCINE; .ALPHA.-TOCOPHEROL; DIPHENYLSILOXY PHENYL TRIMETHICONE; BUTYLATED HYDROXYTOLUENE; SODIUM ALGINATE; HYDROLYZED ORYZANOL OLEATES; HYDROXYPROLINE; SODIUM SUCCINATE ANHYDROUS; SCUTELLARIA BAICALENSIS ROOT; MUCUNA BIRDWOODIANA STEM; CARBOMER HOMOPOLYMER, UNSPECIFIED TYPE; CYDONIA OBLONGA SEED; CRATAEGUS CUNEATA FRUIT; HYALURONATE SODIUM; MARINE NON-GELLING GELATIN; SODIUM LACTATE; MICHELIA CHAMPACA FLOWER; GREEN TEA LEAF; POLYSORBATE 20; SUCCINIC ACID; SOYBEAN; BETULA PLATYPHYLLA BARK; SANDALWOOD; PALMITOYL PENTAPEPTIDE-4

DECORTÉ AQ ABSOLUTE TREATMENT AWAKENING PROTECTIVE DAY CREAM BROAD SPECTRUM SPF 16 SUNSCREEN

Drug Facts

ACTIVE INGREDIENT

Avobenzone 3.00%

Octinoxate 7.49%

Octisalate 1.00%

PURPOSE

Sunscreen

USES

- Helps Prevent Sunburn

DIRECTIONS FOR USE:

- Use in the morning after cleansing skin, or as the final step of your skincare routine. Take an appropriate amount and apply.
- When using foundation, use after applying this product.
- Use a facial cleanser for easy removal.
- lf product enters eyes, rinse with water.
- Close cap after each use.
- Store away from high temperatures.

WARNINGS

For external use only.

Do not useon damaged or broken skin.

WHEN USING

When using this productkeep out of eyes. Rinse with water to remove.

Stop use and ask a doctorif rash occurs.

Keep out of reach of children. If product is swallowed, get medical help or contact a Poison Control Center right away.

DIRECTIONS

For sunscreen use:
• apply liberally 15 minutes before sun exposure
• reapply at least every 2 hours
• use a water resistant sunscreen if swimming or sweating
• Sun Protection Measures.
Spending time in the sun increases your risk of skin cancer and early skin aging. To decrease this risk, regularly use a sunscreen with a Broad Spectrum SPF value of 15 or higher and other sun protection measures including:
• limit time in the sun, especially from 10 a.m. - 2 p.m.
• wear long-sleeved shirts, pants, hats, and sunglasses
• children under 6 months: Ask a doctor

INACTIVE INGREDIENT

Water/AQUA/EAU, Butylene Glycol, Hydrogenated Polydecene, Behenyl Alcohol, Squalane, Polyglyceryl-6 Stearate, Phytosteryl Macadamiate, Glycerin, Caprylic/Capric Triglyceride, Pentylene Glycol, Sorbitol, Glyceryl Stearate SE, Betula Platyphylla Japonica Bark Extract, Betula Platyphylla Japonika Juice, Camellia Sinensis Leaf Extract, Crataegus Cuneata Fruit Extract, Glycine, Glycine Soja (Soybean) Seed Extract, Hydrolyzed Collagen, Hydroxyproline, Michelia Champaca Flower Extract, Mucuna Birdwoodiana Stem Extract, Palmitoyl Pentapeptide-4, Pyrus Cydonia Seed Extract, Santalum Album (Sandalwood) Wood Extract, Scutellaria Baicalensis Root Extract, Sodium Hyaluronate, Tocopherol, Alcohol, Algin, BHT, Carbomer, Dimethicone, Diphenylsiloxy Phenyl Trimethicone, Disodium Succinate, Hydrogenated Lecithin, Phytosteryloleate, Polysorbate 20, Sodium Lactate, Sodium Stearoyl Glutamate, Succinic Acid, Xanthan Gum, Phenoxyethanol, Fragrance (Parfum)

Other information

Protect this product from excessive heat and direct sun

PRINCIPAL DISPLAY PANEL - 45 mL CYLINDER

DECORTÉ AQ

ABSOLUTE TREATMENT AWAKENING PROTECTIVE DAY CREAM BROAD SPECTRUM SPF 16 SUNSCREEN

e 45 mL NET WT. 1.5 OZ.